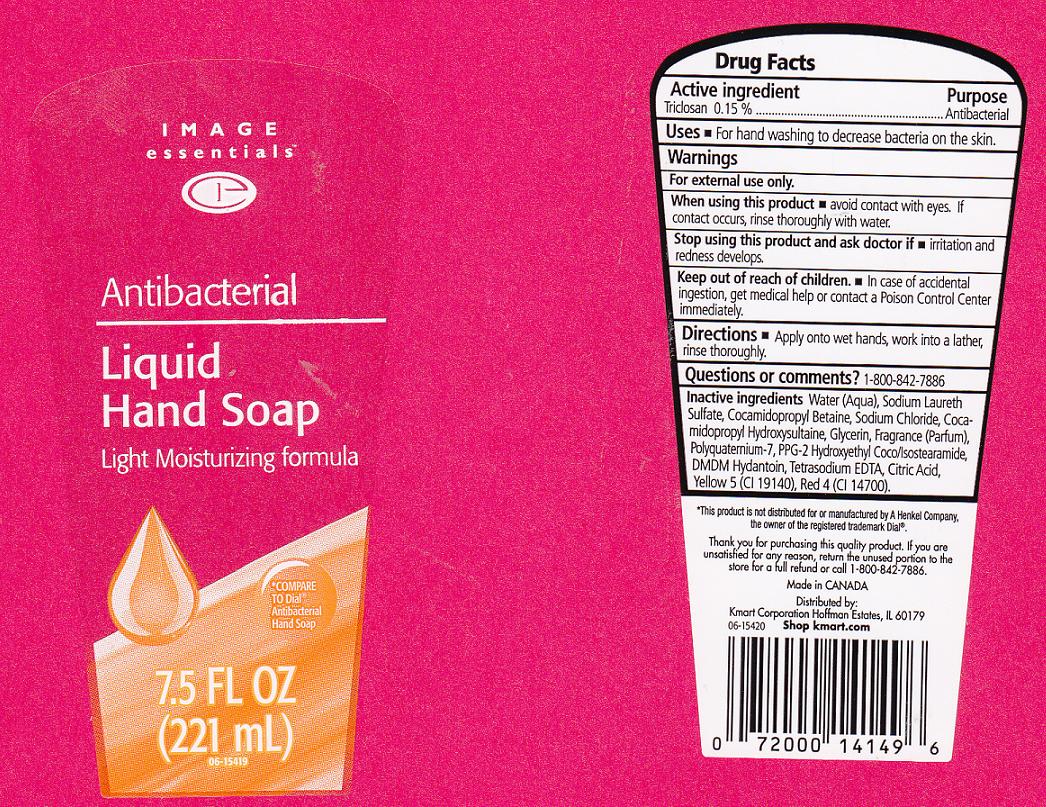 DRUG LABEL: ANTIBACTERIAL 
NDC: 49738-294 | Form: LIQUID
Manufacturer: KMART CORPORATION
Category: otc | Type: HUMAN OTC DRUG LABEL
Date: 20110627

ACTIVE INGREDIENTS: TRICLOSAN 0.15 L/100 L
INACTIVE INGREDIENTS: WATER; SODIUM LAURETH SULFATE; COCAMIDOPROPYL BETAINE; SODIUM CHLORIDE; COCAMIDOPROPYL HYDROXYSULTAINE; GLYCERIN; POLYQUATERNIUM-7 (70/30 ACRYLAMIDE/DADMAC; 1600 KD); DMDM HYDANTOIN; EDETATE SODIUM; ANHYDROUS CITRIC ACID; FD&C YELLOW NO. 5; FD&C RED NO. 4

DRUG FACTS

ACTIVE INGREDIENT

TRICLOSAN 0.15%

PURPOSE

ANTIBACTERIAL

USES

FOR HAND WASHING TO DECREASE BACTERIA ON THE SKIN.

WARNINGS

FOR EXTERNAL USE ONLY.

WHEN USING THIS PRODUCT

AVOID CONTACT WITH EYES. IF CONTACT OCCURS, RINSE THOROUGHLY WITH WATER.

STOP USING THIS PRODUCT AND ASK DOCTOR IF

IRRITATION AND REDNESS DEVELOPS.

KEEP OUT OF REACH OF CHILDREN

IN CASE OF ACCIDENTAL INGESTION, GET MEDICAL HELP OR CONTACT A POISON CONTROL CENTER IMMEDIATELY.

DIRECTIONS

APPLY ONTO WET HANDS, WORK INTO A LATHER, RINSE THOROUGHLY.

QUESTIONS OR COMMENTS

1-800-842-7886

INACTIVE INGREDIENTS

WATER, SODIUM LAURETH SULFATE, COCAMIDROPROPYL BETAINE, SODIUM CHLORIDE, COCAMIDOPROPYL HYDROXYSULTAINE, GLYCERIN, FRAGRANCE, POLYQUATERNIUM-7, PPG-2 HYDROXYETHYL COCO/ISOSTEARAMIDE, DMDM HYDANTOIN, TETRASODIUM EDTA, CITRIC ACID, YELLOW 5 (CI 19140), RED 4 (CI 14700).